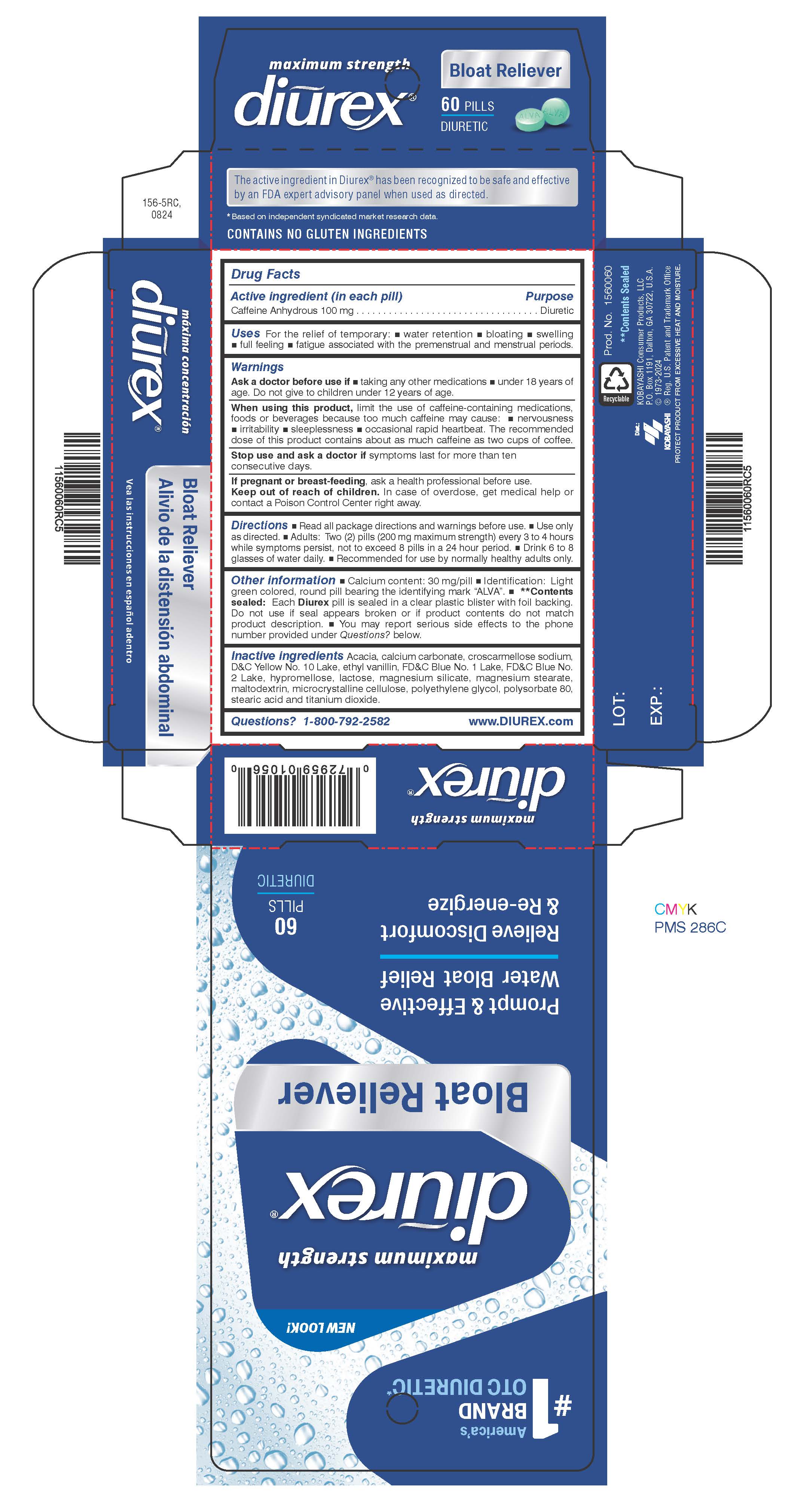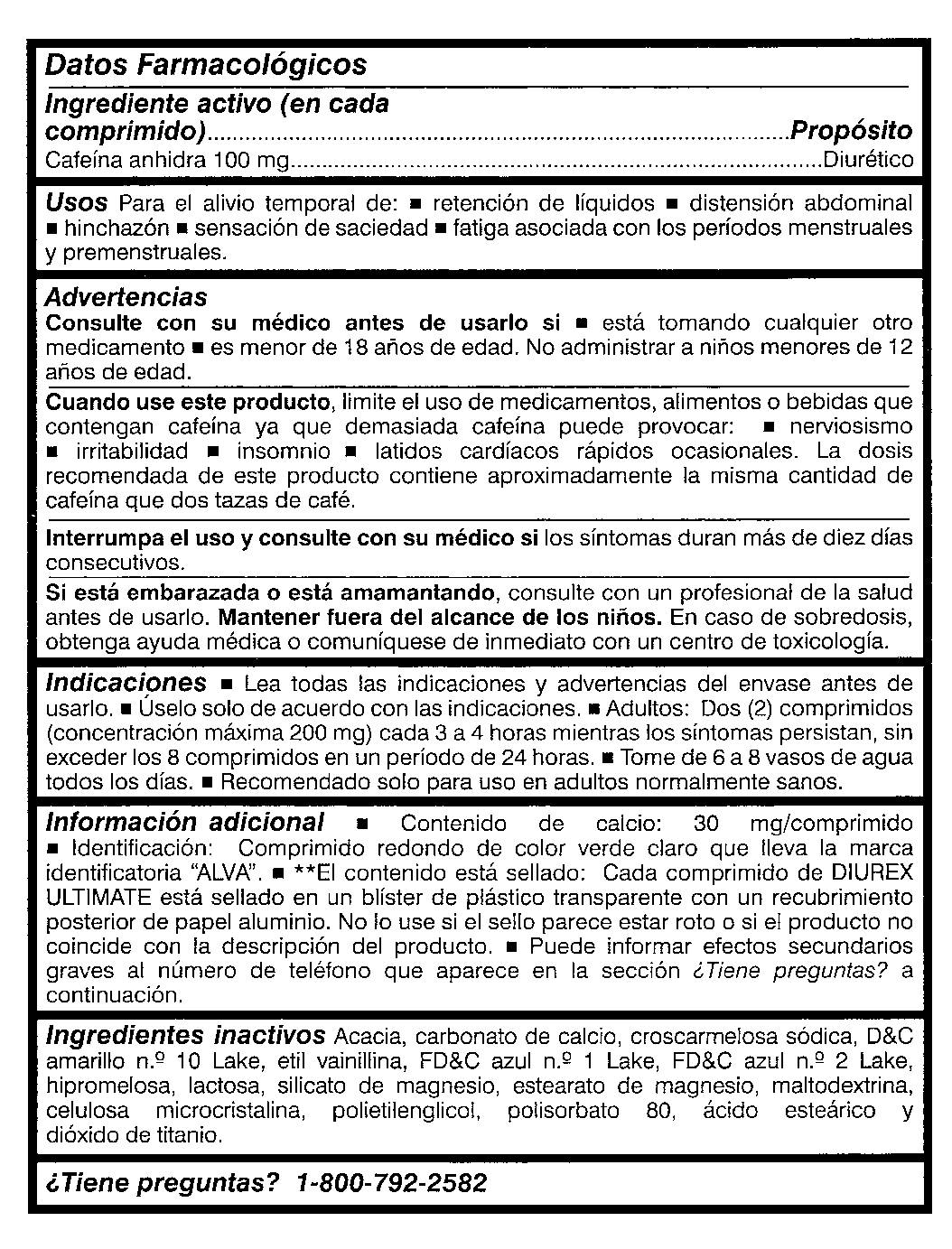 DRUG LABEL: Diurex
NDC: 52389-656 | Form: TABLET, FILM COATED
Manufacturer: Kobayashi Healthcare International, Inc.
Category: otc | Type: HUMAN OTC DRUG LABEL
Date: 20250414

ACTIVE INGREDIENTS: CAFFEINE 100 mg/1 1
INACTIVE INGREDIENTS: CALCIUM CARBONATE; ACACIA; CROSCARMELLOSE SODIUM; ETHYL VANILLIN; D&C YELLOW NO. 10; FD&C BLUE NO. 1; FD&C BLUE NO. 2; HYPROMELLOSES; TALC; MAGNESIUM STEARATE; MALTODEXTRIN; CELLULOSE, MICROCRYSTALLINE; POLYETHYLENE GLYCOL 400; POLYSORBATE 80; STEARIC ACID; TITANIUM DIOXIDE; LACTOSE MONOHYDRATE

Diurex Ultimate

Active ingredient (in each pill)

Caffeine Anhydrous, 100 mg

Purpose

Diuretic

Uses

For the relief of temporary:

- water retention
- bloating
- swelling
- full feeling
- fatigue

associated with the premenstrual and menstrual periods.

Ask a doctor before use if

- taking any other medications
- under 18 years of age. Do not give to children under 12 years of age.

When using this product, limit the use of caffeine-containing medications, foods or beverages because too much caffeine may cause:

- nervousness
- irritability
- sleeplessness
- occasional rapid heart beat.

The recommended dose of this product contains about as much caffeine as two cups of coffee.

Stop use and ask a doctor if symptoms last for more than ten consecutive days.

PREGNANCY OR BREAST FEEDING

If pregnant or breastfeeding, ask a health professional before use.

Keep out of reach of children. In case of overdose, get medical help or contact a Poison Control Center right away.

Directions

- Read all package directions and warnings before use.
- Use only as directed.
- Adults: Two (2) pills (200 mg maximum strength) every 3 to 4 hours wile symptoms persist, not to exceed 8 pills in a 24 hour period.
- Drink 6 to 8 glasses of water daily.
- Recommended for use by normally healthy adults only.

Other information

- Calcium content: 30 mg/pill
- Identification: Light green colored, round pill bearing the identifying mark "ALVA".
- **Contents sealed: Each DIUREX ULTIMATE pill is sealed in a clear plastic blister with foil backing. Do not use if seal appears broken or if product contents do not match product description.
- You may report serious side effects to the phone number provided under Questions? below.

Inactive ingredients

Acacia, calcium carbonate, croscarmellose sodium, D&C Yellow No. 10 Lake, ethyl vanillin, FD&C Blue No. 1 Lake, FD&C Blue No. 2 Lake, hypromellose, lactose, magnesium silicate, magnesium stearate, maltodextrin, microcrystalline cellulose, polyethylene glycol, polysorbate 80, stearic acid, titanium dioxide.

Questions? 1-800-792-2582